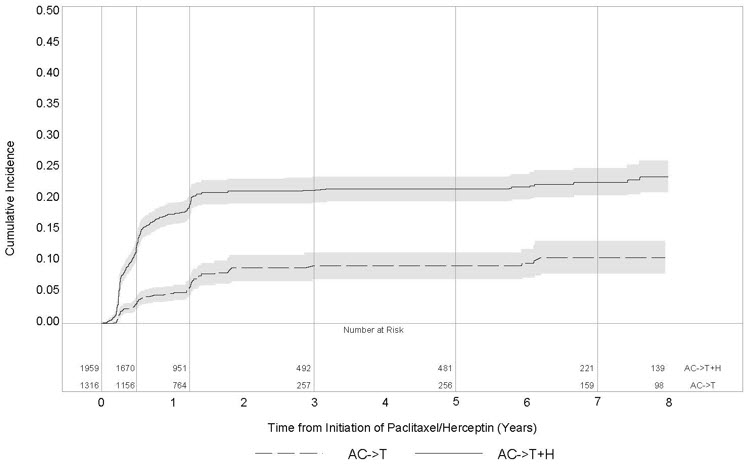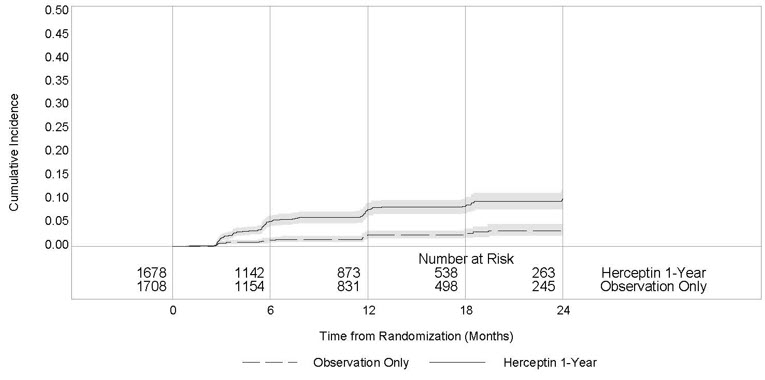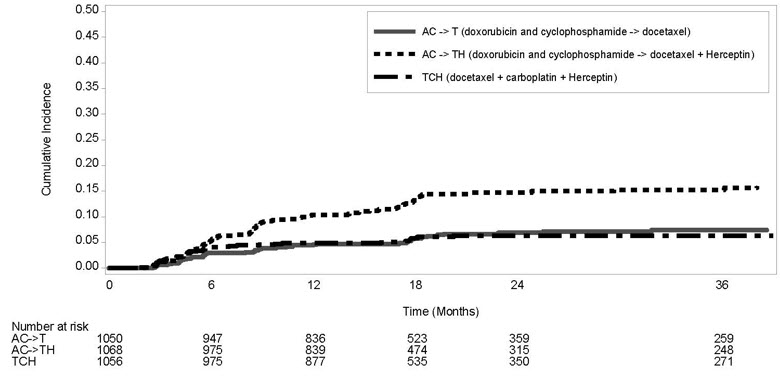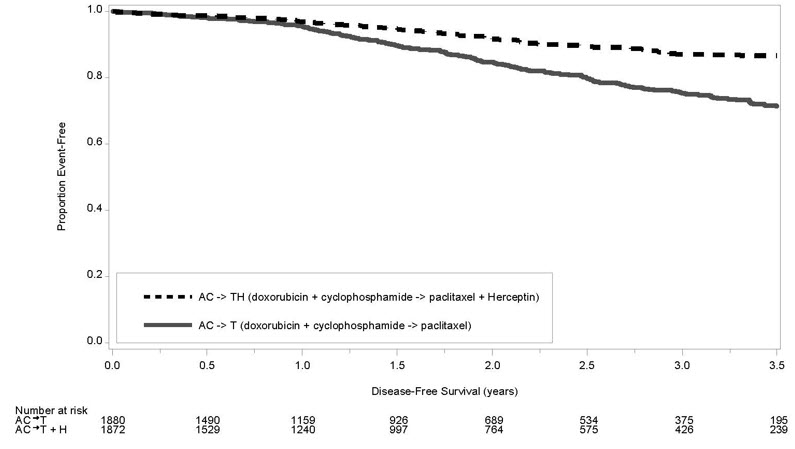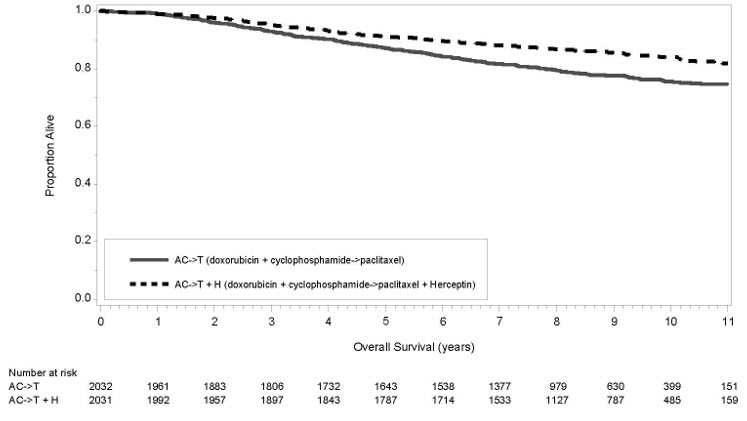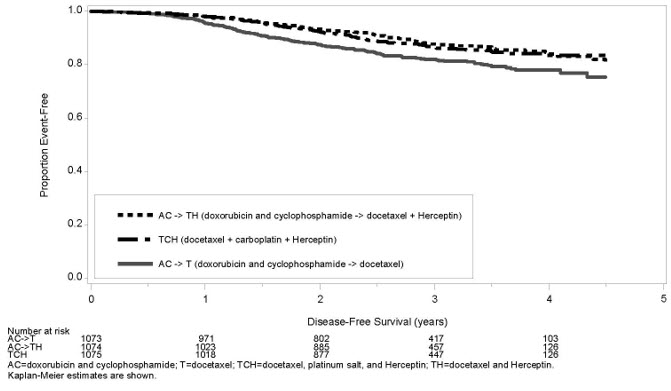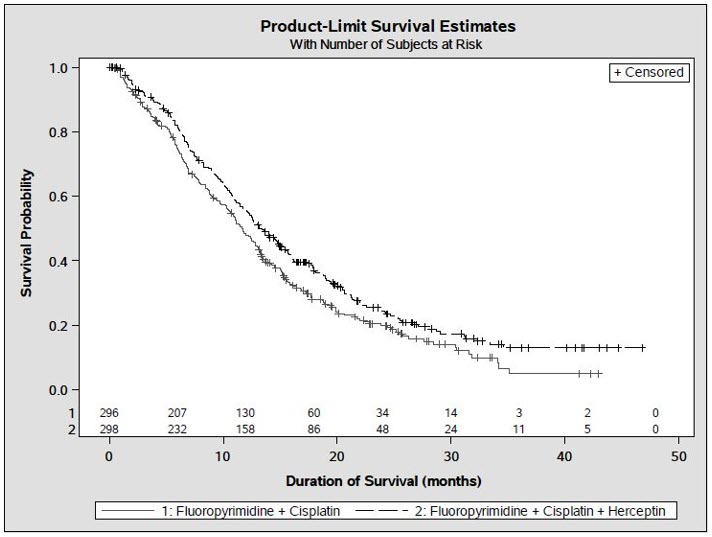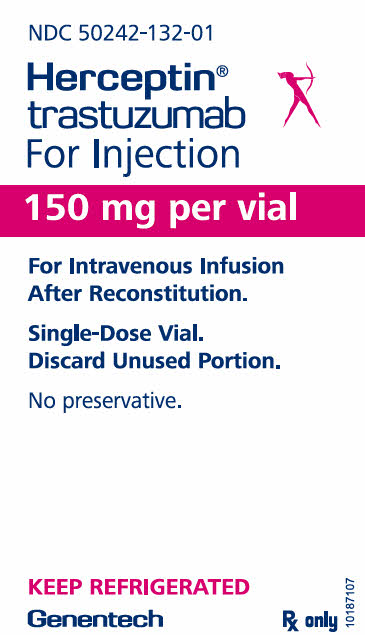 DRUG LABEL: Herceptin
NDC: 50242-132 | Form: INJECTION, POWDER, LYOPHILIZED, FOR SOLUTION
Manufacturer: Genentech, Inc.
Category: prescription | Type: HUMAN PRESCRIPTION DRUG LABEL
Date: 20241118

ACTIVE INGREDIENTS: TRASTUZUMAB 150 mg/7.4 mL
INACTIVE INGREDIENTS: HISTIDINE MONOHYDROCHLORIDE MONOHYDRATE 3.4 mg/7.4 mL; HISTIDINE; TREHALOSE DIHYDRATE; POLYSORBATE 20

HIGHLIGHTS OF PRESCRIBING INFORMATION

These highlights do not include all the information needed to use HERCEPTIN safely and effectively. See full prescribing information for HERCEPTIN.
HERCEPTIN® (trastuzumab) for injection, for intravenous use
Initial U.S. Approval: 1998

WARNING: CARDIOMYOPATHY, INFUSION REACTIONS, EMBRYO-FETAL TOXICITY, and PULMONARY TOXICITY

See full prescribing information for complete boxed warning

Cardiomyopathy: Herceptin can result in subclinical and clinical cardiac failure manifesting as CHF, and decreased LVEF, with greatest risk when administered concurrently with anthracyclines. Evaluate cardiac function prior to and during treatment. Discontinue Herceptin for cardiomyopathy. (2.5, 5.1)

Infusion Reactions, Pulmonary Toxicity: Discontinue Herceptin for anaphylaxis, angioedema, interstitial pneumonitis, or acute respiratory distress syndrome. (5.2, 5.4)

Embryo-Fetal Toxicity: Exposure to Herceptin during pregnancy can result in oligohydramnios, in some cases complicated by pulmonary hypoplasia and neonatal death. Advise patients of these risks and the need for effective contraception. (5.3, 8.1, 8.3)

RECENT MAJOR CHANGES

Dosage and Administration, Evaluation and Testing Before Initiating Herceptin (2.1) | 06/2024

1 INDICATIONS AND USAGE

Herceptin is a HER2/neu receptor antagonist indicated in adults for:

- The treatment of HER2-overexpressing breast cancer. (1.1, 1.2)
- The treatment of HER2-overexpressing metastatic gastric or gastroesophageal junction adenocarcinoma. (1.3)

Select patients for therapy based on an FDA-approved companion diagnostic for Herceptin (1, 2.2).

2 DOSAGE AND ADMINISTRATION

For intravenous (IV) infusion only. Do not administer as an IV push or bolus. Herceptin has different dosage and administration instructions than subcutaneous trastuzumab products. (2.3)

Do not substitute Herceptin (trastuzumab) for or with ado-trastuzumab emtansine or fam-trastuzumab deruxtecan. (2.3)

Perform HER2 testing using FDA-approved tests by laboratories with demonstrated proficiency. (1, 2.2)

Adjuvant Treatment of HER2-Overexpressing Breast Cancer (2.2)

Administer at either:

- Initial dose of 4 mg/kg over 90 minutes IV infusion, then 2 mg/kg over 30 minutes IV infusion weekly for 12 weeks (with paclitaxel or docetaxel) or 18 weeks (with docetaxel and carboplatin). One week after the last weekly dose of Herceptin, administer 6 mg/kg as an IV infusion over 30–90 minutes every three weeks to complete a total of 52 weeks of therapy, or
- Initial dose of 8 mg/kg over 90 minutes IV infusion, then 6 mg/kg over 30–90 minutes IV infusion every three weeks for 52 weeks.

Metastatic HER2-Overexpressing Breast Cancer (2.3)

- Initial dose of 4 mg/kg as a 90 minutes IV infusion followed by subsequent weekly doses of 2 mg/kg as 30 minutes IV infusions.

Metastatic HER2-Overexpressing Gastric Cancer (2.3)

- Initial dose of 8 mg/kg over 90 minutes IV infusion, followed by 6 mg/kg over 30 to 90 minutes IV infusion every 3 weeks.

3 DOSAGE FORMS AND STRENGTHS

- For Injection: 150 mg lyophilized powder in a single-dose vial for reconstitution

4 CONTRAINDICATIONS

- None. (4)

5 WARNINGS AND PRECAUTIONS

- Exacerbation of Chemotherapy-Induced Neutropenia. (5.5, 6.1)

6 ADVERSE REACTIONS

Adjuvant Breast Cancer

- Most common adverse reactions (≥ 5%) are headache, diarrhea, nausea, and chills. (6.1)

Metastatic Breast Cancer

- Most common adverse reactions (≥ 10%) are fever, chills, headache, infection, congestive heart failure, insomnia, cough, and rash. (6.1)

Metastatic Gastric Cancer

- Most common adverse reactions (≥ 10%) are neutropenia, diarrhea, fatigue, anemia, stomatitis, weight loss, upper respiratory tract infections, fever, thrombocytopenia, mucosal inflammation, nasopharyngitis, and dysgeusia. (6.1)

To report SUSPECTED ADVERSE REACTIONS, contact Genentech at 1-888-835-2555 or FDA at 1-800-FDA-1088 or www.fda.gov/medwatch.

8 USE IN SPECIFIC POPULATIONS

Females and Males of Reproductive Potential: Verify the pregnancy status of females prior to initiation of Herceptin (8.3).

FULL PRESCRIBING INFORMATION

WARNING: CARDIOMYOPATHY, INFUSION REACTIONS, EMBRYO-FETAL TOXICITY, and PULMONARY TOXICITY

Cardiomyopathy

Herceptin administration can result in sub-clinical and clinical cardiac failure. The incidence and severity was highest in patients receiving Herceptin with anthracycline-containing chemotherapy regimens.

Evaluate left ventricular function in all patients prior to and during treatment with Herceptin. Discontinue Herceptin treatment in patients receiving adjuvant therapy and withhold Herceptin in patients with metastatic disease for clinically significant decrease in left ventricular function [see Dosage and Administration (2.5) and Warnings and Precautions (5.1)].

Infusion Reactions; Pulmonary Toxicity

Herceptin administration can result in serious and fatal infusion reactions and pulmonary toxicity. Symptoms usually occur during or within 24 hours of Herceptin administration. Interrupt Herceptin infusion for dyspnea or clinically significant hypotension. Monitor patients until symptoms completely resolve. Discontinue Herceptin for anaphylaxis, angioedema, interstitial pneumonitis, or acute respiratory distress syndrome [see Warnings and Precautions (5.2, 5.4)].

Embryo-Fetal Toxicity

Exposure to Herceptin during pregnancy can result in oligohydramnios and oligohydramnios sequence manifesting as pulmonary hypoplasia, skeletal abnormalities, and neonatal death. Advise patients of these risks and the need for effective contraception [see Warnings and Precautions (5.3) and Use in Specific Populations (8.1, 8.3)].

1 INDICATIONS AND USAGE

1.1 Adjuvant Breast Cancer

Herceptin is indicated in adults for adjuvant treatment of HER2 overexpressing node positive or node negative (ER/PR negative or with one high risk feature [see Clinical Studies (14.1)]) breast cancer

- as part of a treatment regimen consisting of doxorubicin, cyclophosphamide, and either paclitaxel or docetaxel
- as part of a treatment regimen with docetaxel and carboplatin
- as a single agent following multi-modality anthracycline based therapy.

Select patients for therapy based on an FDA-approved companion diagnostic for Herceptin [see Dosage and Administration (2.2)].

1.2 Metastatic Breast Cancer

Herceptin is indicated in adults:

- In combination with paclitaxel for first-line treatment of HER2-overexpressing metastatic breast cancer
- As a single agent for treatment of HER2-overexpressing breast cancer in patients who have received one or more chemotherapy regimens for metastatic disease.

Select patients for therapy based on an FDA-approved companion diagnostic for Herceptin [see Dosage and Administration (2.2)].

1.3 Metastatic Gastric Cancer

Herceptin is indicated in adults, in combination with cisplatin and capecitabine or 5-fluorouracil, for the treatment of patients with HER2-overexpressing metastatic gastric or gastroesophageal junction adenocarcinoma who have not received prior treatment for metastatic disease.

Select patients for therapy based on an FDA-approved companion diagnostic for Herceptin [see Dosage and Administration (2.2)].

2 DOSAGE AND ADMINISTRATION

2.1 Evaluation and Testing Before Initiating Herceptin

Assess left ventricular ejection fraction (LVEF) prior to initiation of Herceptin and at regular intervals during treatment. [see Boxed Warning, Dosage and Administration (2.5), Warnings and Precautions (5.1)].

Verify the pregnancy status of females of reproductive potential prior to the initiation of Herceptin [see Warnings and Precautions (5.3), Use in Specific Populations (8.1, 8.3)].

2.2 Patient Selection

Select patients based on HER2 protein overexpression or HER2 gene amplification in tumor specimens [see Indications and Usage (1) and Clinical Studies (14)]. Assessment of HER2 protein overexpression and HER2 gene amplification should be performed using FDA-approved tests specific for breast or gastric cancers by laboratories with demonstrated proficiency. Information on the FDA-approved tests for the detection of HER2 protein overexpression and HER2 gene amplification is available at: http://www.fda.gov/CompanionDiagnostics.

Assessment of HER2 protein overexpression and HER2 gene amplification in metastatic gastric cancer should be performed using FDA-approved tests specifically for gastric cancers due to differences in gastric vs. breast histopathology, including incomplete membrane staining and more frequent heterogeneous expression of HER2 seen in gastric cancers.

Improper assay performance, including use of suboptimally fixed tissue, failure to utilize specified reagents, deviation from specific assay instructions, and failure to include appropriate controls for assay validation, can lead to unreliable results.

2.3 Recommended Dosage

- Herceptin is for intravenous infusion only. Do not administer as an intravenous push or bolus.
- Herceptin has different dosage and administration instructions than subcutaneous trastuzumab products.
- Do not mix Herceptin with other drugs.
- Do not substitute Herceptin (trastuzumab) for or with ado-trastuzumab emtansine or fam-trastuzumab deruxtecan.

Adjuvant Treatment of Breast Cancer

Administer according to one of the following doses and schedules for a total of 52 weeks of Herceptin therapy:

During and following paclitaxel, docetaxel, or docetaxel/carboplatin:

- Initial dose of 4 mg/kg as an intravenous infusion over 90 minutes then at 2 mg/kg as an intravenous infusion over 30 minutes weekly during chemotherapy for the first 12 weeks (paclitaxel or docetaxel) or 18 weeks (docetaxel and carboplatin).
- One week following the last weekly dose of Herceptin, administer Herceptin at 6 mg/kg as an intravenous infusion over 30–90 minutes every three weeks.

As a single agent within three weeks following completion of multi-modality, anthracycline-based chemotherapy regimens:

- Initial dose at 8 mg/kg as an intravenous infusion over 90 minutes
- Subsequent doses at 6 mg/kg as an intravenous infusion over 30–90 minutes every three weeks.
- Extending adjuvant treatment beyond one year is not recommended [see Adverse Reactions (6.1)].

Metastatic Breast Cancer

- Administer Herceptin, alone or in combination with paclitaxel, at an initial dose of 4 mg/kg as a 90-minute intravenous infusion followed by subsequent once weekly doses of 2 mg/kg as 30-minute intravenous infusions until disease progression.

Metastatic Gastric Cancer

- Administer Herceptin at an initial dose of 8 mg/kg as a 90-minute intravenous infusion followed by subsequent doses of 6 mg/kg as an intravenous infusion over 30–90 minutes every three weeks until disease progression.

2.4 Important Dosing Considerations

Missed Dose

If the patient has missed a dose of Herceptin by one week or less, then the usual maintenance dose (weekly schedule: 2 mg/kg; once every three weeks schedule: 6 mg/kg) should be administered as soon as possible. Do not wait until the next planned cycle. Subsequent Herceptin maintenance doses should be administered 7 days or 21 days later according to the weekly or once every three week schedules, respectively.

If the patient has missed a dose of Herceptin by more than one week, a re-loading dose of Herceptin should be administered over approximately 90 minutes (weekly schedule: 4 mg/kg; once every three week schedule: 8 mg/kg) as soon as possible. Subsequent Herceptin maintenance doses (weekly schedule: 2 mg/kg; three-weekly schedule 6 mg/kg) should be administered 7 days or 21 days later according to the weekly or once every three week schedules, respectively.

2.5 Dosage Modifications for Adverse Reactions

Infusion Reactions

[See Boxed Warning, Warnings and Precautions (5.2)]

- Decrease the rate of infusion for mild or moderate infusion reactions
- Interrupt the infusion in patients with dyspnea or clinically significant hypotension
- Discontinue Herceptin for severe or life-threatening infusion reactions.

Cardiomyopathy

[See Boxed Warning, Warnings and Precautions (5.1)]

Assess left ventricular ejection fraction (LVEF) prior to initiation of Herceptin and at regular intervals during treatment. Withhold Herceptin dosing for at least 4 weeks for either of the following:

- ≥ 16% absolute decrease in LVEF from pre-treatment values
- LVEF below institutional limits of normal and ≥ 10% absolute decrease in LVEF from pretreatment values.

Herceptin may be resumed if, within 4–8 weeks, the LVEF returns to normal limits and the absolute decrease from baseline is ≤ 15%.

Permanently discontinue Herceptin for a persistent (> 8 weeks) LVEF decline or for suspension of Herceptin dosing on more than 3 occasions for cardiomyopathy.

2.6 Preparation Instructions

To prevent medication errors, it is important to check the vial labels to ensure that the drug being prepared and administered is Herceptin (trastuzumab) and not ado-trastuzumab emtansine or fam-trastuzumab deruxtecan.

150 mg Single-dose vial

Reconstitution

Reconstitute each 150 mg vial of Herceptin with 7.4 mL of Sterile Water for Injection (SWFI) (not supplied) to yield a single-dose solution containing 21 mg/mL trastuzumab that delivers 7.15 mL (150 mg trastuzumab).

Use appropriate aseptic technique when performing the following reconstitution steps:

- Using a sterile syringe, slowly inject 7.4 mL of SWFI (not supplied) into the vial containing the lyophilized powder of Herceptin, which has a cake-like appearance. The stream of diluent should be directed into the cake. The reconstituted vial yields a solution for single-dose use, containing 21 mg/mL trastuzumab.
- Swirl the vial gently to aid reconstitution. DO NOT SHAKE.
- Slight foaming of the product may be present upon reconstitution. Allow the vial to stand undisturbed for approximately 5 minutes.
- Parenteral drug products should be inspected visually for particulate matter and discoloration prior to administration, whenever solution and container permit. Inspect visually for particulates and discoloration. The solution should be free of visible particulates, clear to slightly opalescent and colorless to pale yellow.
- Use the Herceptin solution immediately following reconstitution with SWFI, as it contains no preservative and is intended for single-dose only. If not used immediately, store the reconstituted Herceptin solution for up to 24 hours at 2°C to 8°C (36°F to 46°F); discard any unused Herceptin after 24 hours. Do not freeze.

Dilution

- Determine the dose (mg) of Herceptin [see Dosage and Administration (2.3)].
- Calculate the volume of the 21 mg/mL reconstituted Herceptin solution needed.
- Withdraw this amount from the vial using a sterile needle and syringe and add it to an infusion bag containing 250 mL of 0.9% Sodium Chloride Injection, USP.
  DO NOT USE DEXTROSE (5%) SOLUTION.
- Gently invert the bag to mix the solution.
- The solution of Herceptin for infusion diluted in polyvinylchloride or polyethylene bags containing 0.9% Sodium Chloride Injection, USP, should be stored at 2°C to 8°C (36°F to 46°F) for no more than 24 hours prior to use. Discard after 24 hours. This storage time is additional to the time allowed for the reconstituted vials. Do not freeze.

3 DOSAGE FORMS AND STRENGTHS

For injection: 150 mg white to pale yellow lyophilized powder in a single-dose vial

4 CONTRAINDICATIONS

None.

5 WARNINGS AND PRECAUTIONS

5.1 Cardiomyopathy

Herceptin can cause left ventricular cardiac dysfunction, arrhythmias, hypertension, disabling cardiac failure, cardiomyopathy, and cardiac death [see Boxed Warning: Cardiomyopathy]. Herceptin can also cause asymptomatic decline in left ventricular ejection fraction (LVEF).

There is a 4–6 fold increase in the incidence of symptomatic myocardial dysfunction among patients receiving Herceptin as a single agent or in combination therapy compared with those not receiving Herceptin. The highest absolute incidence occurs when Herceptin is administered with an anthracycline.

Withhold Herceptin for ≥ 16% absolute decrease in LVEF from pre-treatment values or an LVEF value below institutional limits of normal and ≥ 10% absolute decrease in LVEF from pretreatment values [see Dosage and Administration (2.5)]. The safety of continuation or resumption of Herceptin in patients with Herceptin-induced left ventricular cardiac dysfunction has not been studied. Patients who receive anthracycline after stopping Herceptin may also be at increased risk of cardiac dysfunction [see Drug Interactions (7) and Clinical Pharmacology (12.3)].

Cardiac Monitoring

Conduct thorough cardiac assessment, including history, physical examination, and determination of LVEF by echocardiogram or MUGA scan. The following schedule is recommended:

- Baseline LVEF measurement immediately prior to initiation of Herceptin
- LVEF measurements every 3 months during and upon completion of Herceptin
- Repeat LVEF measurement at 4 week intervals if Herceptin is withheld for significant left ventricular cardiac dysfunction [see Dosage and Administration (2.5)]
- LVEF measurements every 6 months for at least 2 years following completion of Herceptin as a component of adjuvant therapy.

In NSABP B31, 15% (158/1031) of patients discontinued Herceptin due to clinical evidence of myocardial dysfunction or significant decline in LVEF after a median follow-up duration of 8.7 years in the AC-TH arm. In HERA (one-year Herceptin treatment), the number of patients who discontinued Herceptin due to cardiac toxicity at 12.6 months median duration of follow-up was 2.6% (44/1678). In BCIRG006, a total of 2.9% (31/1056) of patients in the TCH arm (1.5% during the chemotherapy phase and 1.4% during the monotherapy phase) and 5.7% (61/1068) of patients in the AC-TH arm (1.5% during the chemotherapy phase and 4.2% during the monotherapy phase) discontinued Herceptin due to cardiac toxicity.

Among 64 patients receiving adjuvant chemotherapy (NSABP B31 and NCCTG N9831) who developed congestive heart failure, one patient died of cardiomyopathy, one patient died suddenly without documented etiology, and 33 patients were receiving cardiac medication at last follow-up. Approximately 24% of the surviving patients had recovery to a normal LVEF (defined as ≥ 50%) and no symptoms on continuing medical management at the time of last follow-up. Incidence of congestive heart failure (CHF) is presented in Table 1. The safety of continuation or resumption of Herceptin in patients with Herceptin-induced left ventricular cardiac dysfunction has not been studied.

Table 1: Incidence of Congestive Heart Failure in Adjuvant Breast Cancer Studies
 |  | Incidence of Congestive Heart Failure % (n)
Study | Regimen | Herceptin | Control
NSABP B31 & NCCTG N9831 [Median follow-up duration for NSABP B31 & NCCTG N9831 combined was 8.3 years in the AC→paclitaxel+Herceptin arm.] | AC [Anthracycline (doxorubicin) and cyclophosphamide.] →Paclitaxel+Herceptin | 3.2% (64/2000) [Includes 1 patient with fatal cardiomyopathy and 1 patient with sudden death without documented etiology.] | 1.3% (21/1655)
HERA [Includes NYHA II-IV and cardiac death at 12.6 months median duration of follow-up in the one-year Herceptin arm.] | Chemotherapy → Herceptin | 2% (30/1678) | 0.3% (5/1708)
BCIRG006 | AC→Docetaxel+Herceptin | 2% (20/1068) | 0.3% (3/1050)
BCIRG006 | Docetaxel+Carboplatin+Herceptin | 0.4% (4/1056) | 0.3% (3/1050)

In HERA (one-year Herceptin treatment), at a median follow-up duration of 8 years, the incidence of severe CHF (NYHA III & IV) was 0.8%, and the rate of mild symptomatic and asymptomatic left ventricular dysfunction was 4.6%.

Table 2: Incidence of Cardiac Dysfunction [Congestive heart failure or significant asymptomatic decrease in LVEF.] in Metastatic Breast Cancer Studies
 |  | Incidence
 |  | NYHA I–IV |  | NYHA III–IV
Study | Event | Herceptin | Control | Herceptin | Control
H0648g (AC) [Anthracycline (doxorubicin or epirubicin) and cyclophosphamide.] | Cardiac Dysfunction | 28% | 7% | 19% | 3%
H0648g (paclitaxel) | Cardiac Dysfunction | 11% | 1% | 4% | 1%
H0649g | Cardiac Dysfunction [Includes 1 patient with fatal cardiomyopathy.] | 7% | N/A | 5% | N/A

In BCIRG006, the incidence of NCI-CTC Grade 3/4 cardiac ischemia/infarction was higher in the Herceptin containing regimens (AC-TH: 0.3% (3/1068) and TCH: 0.2% (2/1056)) as compared to none in AC-T.

5.2 Infusion Reactions

Infusion reactions consist of a symptom complex characterized by fever and chills, and on occasion included nausea, vomiting, pain (in some cases at tumor sites), headache, dizziness, dyspnea, hypotension, rash, and asthenia [see Adverse Reactions (6.1)].

In post-marketing reports, serious and fatal infusion reactions have been reported. Severe reactions, which include bronchospasm, anaphylaxis, angioedema, hypoxia, and severe hypotension, were usually reported during or immediately following the initial infusion. However, the onset and clinical course were variable, including progressive worsening, initial improvement followed by clinical deterioration, or delayed post-infusion events with rapid clinical deterioration. For fatal events, death occurred within hours to days following a serious infusion reaction.

Interrupt Herceptin infusion in all patients experiencing dyspnea, clinically significant hypotension, and intervention of medical therapy administered (which may include epinephrine, corticosteroids, diphenhydramine, bronchodilators, and oxygen). Patients should be evaluated and carefully monitored until complete resolution of signs and symptoms. Permanent discontinuation should be strongly considered in all patients with severe infusion reactions.

There are no data regarding the most appropriate method of identification of patients who may safely be retreated with Herceptin after experiencing a severe infusion reaction. Prior to resumption of Herceptin infusion, the majority of patients who experienced a severe infusion reaction were pre-medicated with antihistamines and/or corticosteroids. While some patients tolerated Herceptin infusions, others had recurrent severe infusion reactions despite pre-medications.

5.3 Embryo-Fetal Toxicity

Herceptin can cause fetal harm when administered to a pregnant woman. In post-marketing reports, use of Herceptin during pregnancy resulted in cases of oligohydramnios and oligohydramnios sequence manifesting as pulmonary hypoplasia, skeletal abnormalities, and neonatal death.

Verify the pregnancy status of females of reproductive potential prior to the initiation of Herceptin. Advise pregnant women and females of reproductive potential that exposure to Herceptin during pregnancy or within 7 months prior to conception can result in fetal harm. Advise females of reproductive potential to use effective contraception during treatment and for 7 months following the last dose of Herceptin [see Use in Specific Populations (8.1, 8.3) and Clinical Pharmacology (12.3)].

5.4 Pulmonary Toxicity

Herceptin use can result in serious and fatal pulmonary toxicity. Pulmonary toxicity includes dyspnea, interstitial pneumonitis, pulmonary infiltrates, pleural effusions, non-cardiogenic pulmonary edema, pulmonary insufficiency and hypoxia, acute respiratory distress syndrome, and pulmonary fibrosis. Such events can occur as sequelae of infusion reactions [see Warnings and Precautions (5.2)]. Patients with symptomatic intrinsic lung disease or with extensive tumor involvement of the lungs, resulting in dyspnea at rest, appear to have more severe toxicity.

5.5 Exacerbation of Chemotherapy-Induced Neutropenia

In randomized, controlled clinical trials, the per-patient incidences of NCI-CTC Grade 3–4 neutropenia and of febrile neutropenia were higher in patients receiving Herceptin in combination with myelosuppressive chemotherapy as compared to those who received chemotherapy alone. The incidence of septic death was similar among patients who received Herceptin and those who did not [see Adverse Reactions (6.1)].

6 ADVERSE REACTIONS

The following adverse reactions are discussed in greater detail in other sections of the label:

- Cardiomyopathy [see Warnings and Precautions (5.1)]
- Infusion Reactions [see Warnings and Precautions (5.2)]
- Embryo-Fetal Toxicity [see Warnings and Precautions (5.3)]
- Pulmonary Toxicity [see Warnings and Precautions (5.4)]
- Exacerbation of Chemotherapy-Induced Neutropenia [see Warnings and Precautions (5.5)]

6.1 Clinical Trials Experience

Because clinical trials are conducted under widely varying conditions, adverse reaction rates observed in the clinical trials of a drug cannot be directly compared to rates in the clinical trials of another drug and may not reflect the rates observed in practice.

The most common adverse reactions in patients receiving Herceptin in the adjuvant and metastatic breast cancer setting are fever, nausea, vomiting, infusion reactions, diarrhea, infections, increased cough, headache, fatigue, dyspnea, rash, neutropenia, anemia, and myalgia. Adverse reactions requiring interruption or discontinuation of Herceptin treatment include CHF, significant decline in left ventricular cardiac function, severe infusion reactions, and pulmonary toxicity [see Dosage and Administration (2.5)].

In the metastatic gastric cancer setting, the most common adverse reactions (≥ 10%) that were increased (≥ 5% difference) in the Herceptin arm as compared to the chemotherapy alone arm were neutropenia, diarrhea, fatigue, anemia, stomatitis, weight loss, upper respiratory tract infections, fever, thrombocytopenia, mucosal inflammation, nasopharyngitis, and dysgeusia.

The most common adverse reactions which resulted in discontinuation of treatment on the Herceptin-containing arm in the absence of disease progression were infection, diarrhea, and febrile neutropenia.

Adjuvant Breast Cancer

The information below reflects exposure to one-year Herceptin therapy across three randomized, open-label studies, Studies 1, 2, and 3, with (n = 3678) or without (n = 3363) trastuzumab in the adjuvant treatment of breast cancer.

HERA

Table 3 reflects exposure to Herceptin in 1678 patients in HERA; the median treatment duration was 51 weeks and median number of infusions was 18 [see Clinical Studies (14.1)].

Table 3: Adverse Reactions (≥1%) in HERA (All Grades) [The incidence of Grade 3 or higher adverse reactions was <1% in both arms for each listed term.]
Adverse Reactions | Herceptin (n = 1678) % | Observation (n = 1708) %
Nervous System
Headache | 10 | 3
Paresthesia | 2 | 0.6
Musculoskeletal
Arthralgia | 8 | 6
Back pain | 5 | 3
Myalgia | 4 | 1
Bone pain | 3 | 2
Muscle spasm | 3 | 0.2
Infections
Nasopharyngitis | 8 | 3
Urinary tract infection | 3 | 0.8
Gastrointestinal
Diarrhea | 7 | 1
Nausea | 6 | 1
Vomiting | 3.5 | 0.6
Constipation | 2 | 1
Dyspepsia | 2 | 0.5
Upper abdominal pain | 2 | 1
General
Pyrexia | 6 | 0.4
Peripheral edema | 5 | 2
Chills | 5 | 0
Asthenia | 4.5 | 2
Influenza-like illness | 2 | 0.2
Respiratory Thoracic Mediastinal
Cough | 5 | 2
Influenza | 4 | 0.5
Dyspnea | 3 | 2
URI | 3 | 1
Rhinitis | 2 | 0.4
Pharyngolaryngeal pain | 2 | 0.5
Sinusitis | 2 | 0.3
Epistaxis | 2 | 0.06
Cardiac
Hypertension | 4 | 2
Dizziness | 4 | 2
Ejection fraction decreased | 3.5 | 0.6
Palpitations | 3 | 0.7
Cardiac arrhythmias [Higher level grouping term.] | 3 | 1
Cardiac failure (congestive) | 2 | 0.3
Skin & Subcutaneous Tissue
Rash | 4 | 0.6
Nail disorders | 2 | 0
Pruritus | 2 | 0.6

Clinically relevant adverse reactions in < 1% of patients who received Herceptin in HERA included hypersensitivity (0.6%), cardiac failure (0.5%), cardiac disorder (0.3%), interstitial pneumonitis (0.2%), pulmonary hypertension (0.2%), ventricular disorder (0.2%), autoimmune thyroiditis (0.3%), and sudden death (0.06%).

Adjuvant Treatment of Breast Cancer with Herceptin Beyond One Year

Extending adjuvant treatment beyond one year is not recommended [see Dosage and Administration (2.2)]. In HERA, a comparison of Herceptin administered once every 3 weeks for two years versus one year was performed. The rate of asymptomatic cardiac dysfunction was increased in the 2-year Herceptin compared to the 1-year Herceptin treatment arm (8.1% versus 4.6%, respectively). More patients experienced at least one adverse reaction of Grade 3 or higher in the 2-year Herceptin treatment arm (20.4%) compared with the one-year Herceptin treatment arm (16.3%).

NSABP B31 and NCCTG N9831

The safety data from NSABP B31 and NCCTG N9831 were obtained from 3655 patients, of whom 2000 received Herceptin; the median treatment duration was 51 weeks [see Clinical Studies (14.1)].

In NSABP B31, only Grade 3–5 adverse events, treatment-related Grade 2 events, and Grade 2–5 dyspnea were collected during and for up to 3 months following protocol-specified treatment. The following non-cardiac adverse reactions of Grade 2–5 occurred at an incidence of at least 2% greater among patients receiving Herceptin plus chemotherapy as compared to chemotherapy alone: fatigue (29.5% vs. 22.4%), infection (24.0% vs. 12.8%), hot flashes (17.1% vs. 15%), anemia (12.3% vs. 6.7%), dyspnea (11.8% vs. 4.6%), rash/desquamation (10.9% vs. 7.6%), leukopenia (10.5% vs. 8.4%), neutropenia (6.4% vs. 4.3%), headache (6.2% vs. 3.8%), pain (5.5% vs. 3%), edema (4.7% vs. 2.7%), and insomnia (4.3% vs. 1.5%). The majority of these events were Grade 2 in severity.

In NCCTG N9831, data collection was limited to the following investigator-attributed treatment-related adverse reactions: NCI-CTC Grade 4 and 5 hematologic toxicities, Grade 3–5 non-hematologic toxicities, selected Grade 2–5 toxicities associated with taxanes (myalgia, arthralgias, nail changes, motor neuropathy, and sensory neuropathy) and Grade 1–5 cardiac toxicities occurring during chemotherapy and/or Herceptin treatment. The following non-cardiac adverse reactions of Grade 2–5 occurred at an incidence of at least 2% greater among patients receiving Herceptin plus chemotherapy as compared to chemotherapy alone: arthralgia (12.2% vs. 9.1%), nail changes (11.5% vs. 6.8%), dyspnea (2.4% vs. 0.2%), and diarrhea (2.2% vs. 0%). The majority of these events were Grade 2 in severity.

BCIRG006

Safety data from BCIRG006 reflect exposure to Herceptin as part of an adjuvant treatment regimen from 2124 patients receiving at least one dose of study treatment [AC-TH: n = 1068; TCH: n = 1056]. The overall median treatment duration was 54 weeks in both the AC-TH and TCH arms. The median number of infusions was 26 in the AC-TH arm and 30 in the TCH arm, including weekly infusions during the chemotherapy phase and once every three week dosing in the monotherapy period [see Clinical Studies (14.1)]. In BCIRG006, the toxicity profile was similar to that reported in Studies NSABP B31, NCCTG N9831, and HERA with the exception of a lower incidence of CHF in the TCH arm.

Metastatic Breast Cancer Studies

The safety of Herceptin was evaluated in one randomized, open-label study (H0648g) of chemotherapy with (n = 235) or without (n = 234) intravenous trastuzumab in patients with metastatic breast cancerand in one single-arm study (H0649g); in patients with metastatic breast cancer (n=222) [see Clinical Studies (14.1)]. Patients received 4 mg/kg initial dose of Herceptin followed by 2 mg/kg weekly. In H0648g, 58% of patients received Herceptin for ≥ 6 months and 9% received Herceptin ≥ 12 months, respectively. In H0649g, 31% of patients received Herceptin for ≥ 6 months and 16% received Herceptin for ≥ 12 months, respectively.

Table 4 shows the adverse reactions (≥ 5%) in patients from H0648g and H0649g.

Table 4: Adverse Reactions ≥ (5%) in the Herceptin Arms in H0648g and H0649g
 | Herceptin [Data for Herceptin single agent were from 4 studies, including 213 patients from H0649g.] n = 352 % | Herceptin + Paclitaxel n = 91 % | Paclitaxel n = 95 % | Herceptin + AC [Anthracycline (doxorubicin or epirubicin) and cyclophosphamide.] n = 143 % | AC n = 135 %
General
Pain | 47 | 61 | 62 | 57 | 42
Asthenia | 42 | 62 | 57 | 54 | 55
Fever | 36 | 49 | 23 | 56 | 34
Chills | 32 | 41 | 4 | 35 | 11
Headache | 26 | 36 | 28 | 44 | 31
Abdominal pain | 22 | 34 | 22 | 23 | 18
Back pain | 22 | 34 | 30 | 27 | 15
Infection | 20 | 47 | 27 | 47 | 31
Flu syndrome | 10 | 12 | 5 | 12 | 6
Accidental injury | 6 | 13 | 3 | 9 | 4
Allergic reaction | 3 | 8 | 2 | 4 | 2
Gastrointestinal
Nausea | 33 | 51 | 9 | 76 | 77
Diarrhea | 25 | 45 | 29 | 45 | 26
Vomiting | 23 | 37 | 28 | 53 | 49
Anorexia | 14 | 24 | 16 | 31 | 26
Nausea and vomiting | 8 | 14 | 11 | 18 | 9
Respiratory
Cough increased | 26 | 41 | 22 | 43 | 29
Dyspnea | 22 | 27 | 26 | 42 | 25
Rhinitis | 14 | 22 | 5 | 22 | 16
Pharyngitis | 12 | 22 | 14 | 30 | 18
Sinusitis | 9 | 21 | 7 | 13 | 6
Skin
Rash | 18 | 38 | 18 | 27 | 17
Herpes simplex | 2 | 12 | 3 | 7 | 9
Acne | 2 | 11 | 3 | 3 | < 1
Nervous
Insomnia | 14 | 25 | 13 | 29 | 15
Dizziness | 13 | 22 | 24 | 24 | 18
Paresthesia | 9 | 48 | 39 | 17 | 11
Depression | 6 | 12 | 13 | 20 | 12
Peripheral neuritis | 2 | 23 | 16 | 2 | 2
Neuropathy | 1 | 13 | 5 | 4 | 4
Metabolic
Peripheral edema | 10 | 22 | 20 | 20 | 17
Edema | 8 | 10 | 8 | 11 | 5
Cardiovascular
Congestive heart failure | 7 | 11 | 1 | 28 | 7
Tachycardia | 5 | 12 | 4 | 10 | 5
Musculoskeletal
Bone pain | 7 | 24 | 18 | 7 | 7
Arthralgia | 6 | 37 | 21 | 8 | 9
Urogenital
Urinary tract infection | 5 | 18 | 14 | 13 | 7
Blood and Lymphatic
Anemia | 4 | 14 | 9 | 36 | 26
Leukopenia | 3 | 24 | 17 | 52 | 34

Metastatic Gastric Cancer

The safety of Herceptin was evaluated in patients with previously untreated for metastatic gastric or gastroesophageal junction adenocarcinoma in an open label, multi-center trial (ToGA) [see Clinical Studies (14.3)]. Patients were randomized (1:1) to receive Herceptin in combination with cisplatin and a fluoropyrimidine (FC+H) (n=294) or chemotherapy alone (FC) (n=290) Patients in the Herceptin plus chemotherapy arm received Herceptin 8 mg/kg administered on Day 1 (prior to chemotherapy) followed by 6 mg/kg every 21 days until disease progression. Cisplatin was administered at 80 mg/m^2 on Day 1 and the fluoropyrimidine was administered as either capecitabine 1000 mg/m^2 orally twice a day on Days 1–14 or 5-fluorouracil 800 mg/m^2/day as a continuous intravenous infusion Days 1 through 5. Chemotherapy was administered for six 21-day cycles. Median duration of Herceptin treatment was 21 weeks and the median number of Herceptin infusions administered was eight.

Table 5: Adverse Reactions (All Grades ≥ 5% or Grade 3-4 ≥ 1% between Arms) in ToGA
Adverse Reactions | Herceptin +FC (N = 294) % |  | FC (N = 290) %
 | All Grades | Grades 3-4 | All Grades | Grades 3-4
Investigations
Neutropenia | 78 | 34 | 73 | 29
Hypokalemia | 28 | 10 | 24 | 6
Anemia | 28 | 12 | 21 | 10
Thrombocytopenia | 16 | 5 | 11 | 3
Blood and Lymphatic System Disorders
Febrile Neutropenia | — | 5 | — | 3
Gastrointestinal Disorders
Diarrhea | 37 | 9 | 28 | 4
Stomatitis | 24 | 1 | 15 | 2
Dysphagia | 6 | 2 | 3 | < 1
General
Fatigue | 35 | 4 | 28 | 2
Fever | 18 | 1 | 12 | 0
Mucosal Inflammation | 13 | 2 | 6 | 1
Chills | 8 | < 1 | 0 | 0
Metabolism and Nutrition Disorders
Weight Decrease | 23 | 2 | 14 | 2
Infections and Infestations
Upper Respiratory Tract Infections | 19 | 0 | 10 | 0
Nasopharyngitis | 13 | 0 | 6 | 0
Renal and Urinary Disorders
Renal Failure and Impairment | 18 | 3 | 15 | 2
Nervous System Disorders
Dysgeusia | 10 | 0 | 5 | 0

The following subsections provide additional detail regarding adverse reactions observed in clinical trials of adjuvant breast cancer, metastatic breast cancer, metastatic gastric cancer, or post-marketing experience.

Cardiomyopathy

Serial measurement of cardiac function (LVEF) was obtained in clinical trials in the adjuvant treatment of breast cancer. In HERA, the median duration of follow-up was 12.6 months (12.4 months in the observation arm; 12.6 months in the 1-year Herceptin arm); and in NSABP B31 and NCCTG N9831, 7.9 years in the AC-T arm, 8.3 years in the AC-TH arm. Following initiation of Herceptin therapy, the incidence of new-onset dose-limiting myocardial dysfunction was higher among patients receiving Herceptin and paclitaxel as compared to those receiving paclitaxel alone in NSABP B31 and NCCTG N9831, and in patients receiving one-year Herceptin monotherapy compared to observation in HERA (see Table 6, Figures 1 and 2). The incidence of new-onset cardiac dysfunction, as measured by LVEF, remained similar when compared to the analysis performed at a median follow-up of 2.0 years in the AC-TH arm. This analysis showed evidence of reversibility of left ventricular dysfunction, with 64.5% of patients who experienced symptomatic CHF in the AC-TH group being asymptomatic at latest follow-up, and 90.3% having full or partial LVEF recovery.

Table 6: Myocardial Dysfunction (by LVEF) in Studies 1, 2, 3 and 4 [For Studies 1, 2 and 3, events are counted from the beginning of Herceptin treatment. For BCIRG006, events are counted from the date of randomization.]
Study and Arm | LVEF < 50% and Decrease from Baseline |  |  | LVEF Decrease
Study and Arm | LVEF < 50% | ≥ 10% decrease | ≥ 16% decrease | < 20% and ≥ 10% | ≥ 20%
Studies 1 & 2 [NSABP B31 and NCCTG N9831 regimens: doxorubicin and cyclophosphamide followed by paclitaxel (AC→T) or paclitaxel plus Herceptin (AC→TH).] , [Median duration of follow-up for NSABP B31 and NCCTG N9831 combined was 8.3 years in the AC→TH arm.]
AC→TH (n = 1856) | 23.1% (428) | 18.5% (344) | 11.2% (208) | 37.9% (703) | 8.9% (166)
AC→T (n = 1170) | 11.7% (137) | 7.0% (82) | 3.0% (35) | 22.1% (259) | 3.4% (40)
HERA [Median follow-up duration of 12.6 months in the one-year Herceptin treatment arm.]
Herceptin (n = 1678) | 8.6% (144) | 7.0% (118) | 3.8% (64) | 22.4% (376) | 3.5% (59)
Observation (n = 1708) | 2.7% (46) | 2.0% (35) | 1.2% (20) | 11.9% (204) | 1.2% (21)
BCIRG006 [BCIRG006 regimens: doxorubicin and cyclophosphamide followed by docetaxel (AC→T) or docetaxel plus Herceptin (AC→TH); docetaxel and carboplatin plus Herceptin (TCH).]
TCH (n = 1056) | 8.5% (90) | 5.9% (62) | 3.3% (35) | 34.5% (364) | 6.3% (67)
AC→TH (n = 1068) | 17% (182) | 13.3% (142) | 9.8% (105) | 44.3% (473) | 13.2% (141)
AC→T (n = 1050) | 9.5% (100) | 6.6% (69) | 3.3% (35) | 34% (357) | 5.5% (58)

Figure 1
NSABP B31 and NCCTG N9831: Cumulative Incidence of Time to First LVEF
Decline of ≥ 10 Percentage Points from Baseline and to Below 50% with Death as a Competing Risk Event

Time 0 is initiation of paclitaxel or Herceptin + paclitaxel therapy.

Figure 2
HERA: Cumulative Incidence of Time to First LVEF
Decline of ≥ 10 Percentage Points from Baseline and to Below 50% with Death as a Competing Risk Event

Time 0 is the date of randomization.

Figure 3
BCIRG006: Cumulative Incidence of Time to First LVEF
Decline of ≥ 10 Percentage Points from Baseline and to Below 50% with Death as a Competing Risk Event

Time 0 is the date of randomization.

The incidence of congestive heart failure among patients in the metastatic breast cancer trials was classified for severity using the New York Heart Association classification system (I–IV, where IV is the most severe level of cardiac failure) (see Table 2). In the metastatic breast cancer trials, the probability of cardiac dysfunction was highest in patients who received Herceptin concurrently with anthracyclines.

In ToGA, 5% of patients in the Herceptin plus chemotherapy arm compared to 1.1% of patients in the chemotherapy alone arm had LVEF value below 50% with a ≥ 10% absolute decrease in LVEF from pretreatment values.

Infusion Reactions

During the first infusion with Herceptin, the symptoms most commonly reported were chills and fever, occurring in approximately 40% of patients in clinical trials. Symptoms were treated with acetaminophen, diphenhydramine, and meperidine (with or without reduction in the rate of Herceptin infusion); permanent discontinuation of Herceptin for infusion reactions was required in < 1% of patients. Other signs and/or symptoms may include nausea, vomiting, pain (in some cases at tumor sites), rigors, headache, dizziness, dyspnea, hypotension, elevated blood pressure, rash, and asthenia. Infusion reactions occurred in 21% and 35% of patients, and were severe in 1.4% and 9% of patients, on second or subsequent Herceptin infusions administered as monotherapy or in combination with chemotherapy, respectively. In the post-marketing setting, severe infusion reactions, including hypersensitivity, anaphylaxis, and angioedema have been reported.

Anemia

In randomized controlled clinical trials, the overall incidence of anemia (30% vs. 21% [H0648g]), of selected NCI-CTC Grade 2–5 anemia (12.3% vs. 6.7% [NSABP B31]), and of anemia requiring transfusions (0.1% vs. 0 patients [NCCTG N9831]) were increased in patients receiving Herceptin and chemotherapy compared with those receiving chemotherapy alone. Following the administration of Herceptin as a single agent (H0649g), the incidence of NCI-CTC Grade 3 anemia was < 1%. In ToGA (metastatic gastric cancer), on the Herceptin containing arm as compared to the chemotherapy alone arm, the overall incidence of anemia was 28% compared to 21% and of NCI- CTC Grade 3/4 anemia was 12.2% compared to 10.3%.

Neutropenia

In randomized controlled clinical trials in the adjuvant setting, the incidence of selected NCI-CTC Grade 4–5 neutropenia (1.7% vs. 0.8% [NCCTG N9831]) and of selected Grade 2–5 neutropenia (6.4% vs. 4.3% [NSABP B31]) were increased in patients receiving Herceptin and chemotherapy compared with those receiving chemotherapy alone. In a randomized, controlled trial in patients with metastatic breast cancer, the incidences of NCI-CTC Grade 3/4 neutropenia (32% vs. 22%) and of febrile neutropenia (23% vs. 17%) were also increased in patients randomized to Herceptin in combination with myelosuppressive chemotherapy as compared to chemotherapy alone. In ToGA (metastatic gastric cancer) on the Herceptin containing arm as compared to the chemotherapy alone arm, the incidence of NCI-CTC Grade 3/4 neutropenia was 36.8% compared to 28.9%; febrile neutropenia 5.1% compared to 2.8%.

Infection

The overall incidences of infection (46% vs. 30% [H0648g]), of selected NCI-CTC Grade 2–5 infection/febrile neutropenia (24.3% vs. 13.4% [NSABP B31]) and of selected Grade 3–5 infection/febrile neutropenia (2.9% vs. 1.4% [NCCTG N9831]) were higher in patients receiving Herceptin and chemotherapy compared with those receiving chemotherapy alone. The most common site of infections in the adjuvant setting involved the upper respiratory tract, skin, and urinary tract.

In BCIRG006, the overall incidence of infection was higher with the addition of Herceptin to AC-T but not to TCH [44% (AC-TH), 37% (TCH), 38% (AC-T)]. The incidences of NCI-CTC Grade 3–4 infection were similar [25% (AC-TH), 21% (TCH), 23% (AC-T)] across the three arms.

In a randomized, controlled trial in treatment of metastatic breast cancer, the reported incidence of febrile neutropenia was higher (23% vs. 17%) in patients receiving Herceptin in combination with myelosuppressive chemotherapy as compared to chemotherapy alone.

Pulmonary Toxicity

Adjuvant Breast Cancer

Among women receiving adjuvant therapy for breast cancer, the incidence of selected NCI-CTC Grade 2–5 pulmonary toxicity (14.3% vs. 5.4% [NSABP B31]) and of selected NCI-CTC Grade 3–5 pulmonary toxicity and spontaneous reported Grade 2 dyspnea (3.4% vs. 0.9% [NCCTG N9831]) was higher in patients receiving Herceptin and chemotherapy compared with chemotherapy alone. The most common pulmonary toxicity was dyspnea (NCI-CTC Grade 2–5: 11.8% vs. 4.6% [NSABP B31]; NCI-CTC Grade 2–5: 2.4% vs. 0.2% [NCCTG N9831]).

Pneumonitis/pulmonary infiltrates occurred in 0.7% of patients receiving Herceptin compared with 0.3% of those receiving chemotherapy alone. Fatal respiratory failure occurred in 3 patients receiving Herceptin, one as a component of multi-organ system failure, as compared to 1 patient receiving chemotherapy alone.

In HERA, there were 4 cases of interstitial pneumonitis in the one-year Herceptin treatment arm compared to none in the observation arm at a median follow-up duration of 12.6 months.

Metastatic Breast Cancer

Among women receiving Herceptin for treatment of metastatic breast cancer, the incidence of pulmonary toxicity was also increased. Pulmonary adverse events have been reported in the post-marketing experience as part of the symptom complex of infusion reactions. Pulmonary events include bronchospasm, hypoxia, dyspnea, pulmonary infiltrates, pleural effusions, non-cardiogenic pulmonary edema, and acute respiratory distress syndrome. For a detailed description, see Warnings and Precautions (5.4).

Thrombosis/Embolism

In 4 randomized, controlled clinical trials, the incidence of thrombotic adverse events was higher in patients receiving Herceptin and chemotherapy compared to chemotherapy alone in three studies (2.6% vs. 1.5% [NSABP B31], 2.5% and 3.7% vs. 2.2% [BCIRG006] and 2.1% vs. 0% [H0648g]).

Diarrhea

Among women receiving adjuvant therapy for breast cancer, the incidence of NCI-CTC Grade 2–5 diarrhea (6.7% vs. 5.4% [NSABP B31]) and of NCI-CTC Grade 3–5 diarrhea (2.2% vs. 0% [NCCTG N9831]), and of Grade 1–4 diarrhea (7% vs. 1% [HERA; one-year Herceptin treatment at 12.6 months median duration of follow-up]) were higher in patients receiving Herceptin as compared to controls. In BCIRG006, the incidence of Grade 3–4 diarrhea was higher [5.7% AC-TH, 5.5% TCH vs. 3.0% AC-T] and of Grade 1–4 was higher [51% AC-TH, 63% TCH vs. 43% AC-T] among women receiving Herceptin. Of patients receiving Herceptin as a single agent for the treatment of metastatic breast cancer, 25% experienced diarrhea. An increased incidence of diarrhea was observed in patients receiving Herceptin in combination with chemotherapy for treatment of metastatic breast cancer.

Renal Toxicity

In ToGA (metastatic gastric cancer) on the Herceptin-containing arm as compared to the chemotherapy alone arm the incidence of renal impairment was 18% compared to 14.5%. Severe (Grade 3/4) renal failure was 2.7% on the Herceptin-containing arm compared to 1.7% on the chemotherapy only arm. Treatment discontinuation for renal insufficiency/failure was 2% on the Herceptin-containing arm and 0.3% on the chemotherapy only arm.

In the post-marketing setting, rare cases of nephrotic syndrome with pathologic evidence of glomerulopathy have been reported. The time to onset ranged from 4 months to approximately 18 months from initiation of Herceptin therapy. Pathologic findings included membranous glomerulonephritis, focal glomerulosclerosis, and fibrillary glomerulonephritis. Complications included volume overload and congestive heart failure.

6.2 Post-Marketing Experience

The following adverse reactions have been identified during post-approval use of Herceptin. Because these reactions are reported voluntarily from a population of uncertain size, it is not always possible to reliably estimate their frequency or establish a causal relationship to drug exposure.

- Infusion reaction [see Warnings and Precautions (5.2)]
- Oligohydramnios or oligohydramnios sequence, including pulmonary hypoplasia, skeletal abnormalities, and neonatal death [see Warnings and Precautions (5.3)]
- Glomerulopathy [see Adverse Reactions (6.1)]
- Immune thrombocytopenia
- Tumor lysis syndrome (TLS): Cases of possible TLS have been reported in patients treated with Herceptin. Patients with significant tumor burden (e.g. bulky metastases) may be at a higher risk. Patients could present with hyperuricemia, hyperphosphatemia, and acute renal failure which may represent possible TLS. Providers should consider additional monitoring and/or treatment as clinically indicated.

7 DRUG INTERACTIONS

Anthracyclines

Patients who receive anthracycline after stopping Herceptin may be at increased risk of cardiac dysfunction because of trastuzumab's estimated long washout period [see Clinical Pharmacology (12.3)]. If possible, avoid anthracycline-based therapy for up to 7 months after stopping Herceptin. If anthracyclines are used, closely monitor the patient's cardiac function.

8 USE IN SPECIFIC POPULATIONS

8.1 Pregnancy

Pregnancy Pharmacovigilance Program

There is a pregnancy pharmacovigilance program for Herceptin. If Herceptin is administered during pregnancy, or if a patient becomes pregnant while receiving Herceptin or within 7 months following the last dose of Herceptin, health care providers and patients should immediately report Herceptin exposure to Genentech at 1-888-835-2555.

Risk Summary

Herceptin can cause fetal harm when administered to a pregnant woman. In post-marketing reports and published literature, use of Herceptin during pregnancy resulted in cases of oligohydramnios and of oligohydramnios sequence, manifesting as pulmonary hypoplasia, skeletal abnormalities, and neonatal death [see Data]. Apprise the patient of the potential risks to a fetus. There are clinical considerations if Herceptin is used in a pregnant woman or if a patient becomes pregnant within 7 months following the last dose of Herceptin [see Clinical Considerations].

The background risk of major birth defects and miscarriage for the indicated population is unknown. In the U.S. general population, the estimated background risk of major birth defects and miscarriage in clinically recognized pregnancies is 2% to 4% and 15% to 20%, respectively.

Clinical Considerations

Fetal/Neonatal Adverse Reactions

Monitor women who received Herceptin during pregnancy or within 7 months prior to conception for oligohydramnios. If oligohydramnios occurs, perform fetal/neonatal testing that is appropriate for gestational age and consistent with community standards of care.

Data

Human Data

In post-marketing reports and published literature, use of Herceptin during pregnancy resulted in cases of oligohydramnios and of oligohydramnios sequence. Fetal manifestations included pulmonary hypoplasia, skeletal abnormalities, and neonatal death. These case reports described oligohydramnios in pregnant women who received Herceptin either alone or in combination with chemotherapy. In most reported cases, amniotic fluid index increased after Herceptin was stopped. In reported cases where Herceptin therapy was resumed after amniotic index improved, oligohydramnios recurred.

Animal Data

In studies where trastuzumab was administered to pregnant Cynomolgus monkeys during the period of organogenesis at doses up to 25 mg/kg given twice weekly (up to 25 times the recommended weekly human dose of 2 mg/kg), trastuzumab crossed the placental barrier during the early (Gestation Days 20 to 50) and late (Gestation Days 120 to 150) phases of gestation. The resulting concentrations of trastuzumab in fetal serum and amniotic fluid were approximately 33% and 25%, respectively, of those present in the maternal serum but were not associated with adverse developmental effects.

8.2 Lactation

Risk Summary

There is no information regarding the presence of trastuzumab in human milk, the effects on the breastfed infant, or the effects on milk production. Published data suggest human IgG is present in human milk but does not enter the neonatal and infant circulation in substantial amounts. Trastuzumab was present in the milk of lactating Cynomolgus monkeys but not associated with neonatal toxicity [see Data]. Consider the developmental and health benefits of breastfeeding along with the mother's clinical need for Herceptin treatment and any potential adverse effects on the breastfed child from Herceptin or from the underlying maternal condition. This consideration should also take into account the trastuzumab wash out period of 7 months [see Clinical Pharmacology (12.3)].

Data

In lactating Cynomolgus monkeys, trastuzumab was present in breast milk at about 0.3% of maternal serum concentrations after pre- (beginning Gestation Day 120) and post-partum (through Post-partum Day 28) doses of 25 mg/kg administered twice weekly (25 times the recommended weekly human dose of 2 mg/kg of Herceptin). Infant monkeys with detectable serum levels of trastuzumab did not exhibit any adverse effects on growth or development from birth to 1 month of age.

8.3 Females and Males of Reproductive Potential

Pregnancy Testing

Verify the pregnancy status of females of reproductive potential prior to the initiation of Herceptin.

Contraception

Females

Herceptin can cause embryo-fetal harm when administered during pregnancy. Advise females of reproductive potential to use effective contraception during treatment with Herceptin and for 7 months following the last dose of Herceptin [see Use in Specific Populations (8.1) and Clinical Pharmacology (12.3)].

8.4 Pediatric Use

The safety and effectiveness of Herceptin in pediatric patients have not been established.

8.5 Geriatric Use

Herceptin has been administered to 386 patients who were 65 years of age or over (253 in the adjuvant treatment and 133 in metastatic breast cancer treatment settings). The risk of cardiac dysfunction was increased in geriatric patients as compared to younger patients in both those receiving treatment for metastatic disease in H0648g and H0649g, or adjuvant therapy in NSABP B31 and NCCTG N9831. Limitations in data collection and differences in study design of the 4 studies of Herceptin in adjuvant treatment of breast cancer preclude a determination of whether the toxicity profile of Herceptin in older patients is different from younger patients. The reported clinical experience is not adequate to determine whether the efficacy improvements (ORR, TTP, OS, DFS) of Herceptin treatment in older patients is different from that observed in patients < 65 years of age for metastatic disease and adjuvant treatment.

In ToGA (metastatic gastric cancer), of the 294 patients treated with Herceptin, 108 (37%) were 65 years of age or older, while 13 (4.4%) were 75 and over. No overall differences in safety or effectiveness were observed.

11 DESCRIPTION

Trastuzumab is a humanized IgG1 kappa monoclonal antibody that selectively binds with high affinity to the extracellular domain of the human epidermal growth factor receptor 2 protein, HER2. Trastuzumab is produced by recombinant DNA technology in a mammalian cell (Chinese Hamster Ovary) culture.

Herceptin (trastuzumab) for injection is a sterile, white to pale yellow, preservative-free lyophilized powder with a cake-like appearance, for intravenous administration.

Each single-dose vial of Herceptin delivers 150 mg trastuzumab, 136.2 mg α,α-trehalose dihydrate, 3.4 mg L-histidine HCl monohydrate, 2.2 mg L-histidine, and 0.6 mg polysorbate 20. Reconstitution with 7.4 mL of sterile water for injection (SWFI) yields a solution containing 21 mg/mL trastuzumab that delivers 7.15 mL (150 mg trastuzumab), at a pH of approximately 6.

12 CLINICAL PHARMACOLOGY

12.1 Mechanism of Action

The HER2 (or c-erbB2) proto-oncogene encodes a transmembrane receptor protein of 185 kDa, which is structurally related to the epidermal growth factor receptor. Herceptin has been shown, in both in vitro assays and in animals, to inhibit the proliferation of human tumor cells that overexpress HER2.

Herceptin is a mediator of antibody-dependent cellular cytotoxicity (ADCC). In vitro, Herceptin-mediated ADCC has been shown to be preferentially exerted on HER2 overexpressing cancer cells compared with cancer cells that do not overexpress HER2.

12.2 Pharmacodynamics

Herceptin exposure-response relationships and the time course of pharmacodynamic responses are not fully characterized.

Cardiac Electrophysiology

The effects of trastuzumab on electrocardiographic (ECG) endpoints, including QTc interval duration, were evaluated in patients with HER2 positive solid tumors. Trastuzumab had no clinically relevant effect on the QTc interval duration and there was no apparent relationship between serum trastuzumab concentrations and change in QTcF interval duration in patients with HER2 positive solid tumors.

12.3 Pharmacokinetics

The pharmacokinetics of trastuzumab was evaluated in a pooled population pharmacokinetic (PK) model analysis of 1,582 subjects with primarily breast cancer and metastatic gastric cancer (MGC) receiving intravenous Herceptin. Total trastuzumab clearance increases with decreasing concentrations due to parallel linear and non-linear elimination pathways.

Although the average trastuzumab exposure was higher following the first cycle in breast cancer patients receiving the once every three week schedule compared to the weekly schedule of Herceptin, the average steady-state exposure was essentially the same at both dosages. The average trastuzumab exposure following the first cycle and at steady state as well as the time to steady state was higher in breast cancer patients compared to MGC patients at the same dosage; however, the reason for this exposure difference is unknown. Additional predicted trastuzumab exposure and PK parameters following the first Herceptin cycle and at steady state exposure are described in Tables 7 and 8, respectively.

Population PK based simulations indicate that following discontinuation of Herceptin, concentrations in at least 95% of breast cancer and MGC patients will decrease to approximately 3% of the population predicted steady-state trough serum concentration (approximately 97% washout) by 7 months [see Warnings and Precautions (5.1) and Use in Specific Populations (8.1, 8.3)].

Table 7 Population Predicted Cycle 1 PK Exposures (Median with 5th – 95th Percentiles) in Breast Cancer and MGC Patients
Schedule | Primary tumor type | N | Cmin (µg/mL) | Cmax (µg/mL) | AUC0-21days (µg.day/mL)
8 mg/kg + 6 mg/kg q3w | Breast cancer | 1195 | 29.4 (5.8 - 59.5) | 178 (117 - 291) | 1373 (736 - 2245)
8 mg/kg + 6 mg/kg q3w | MGC | 274 | 23.1 (6.1 - 50.3) | 132 (84.2 - 225) | 1109 (588 - 1938)
4 mg/kg + 2 mg/kg qw | Breast cancer | 1195 | 37.7 (12.3 - 70.9) | 88.3 (58 - 144) | 1066 (586 - 1754)

Table 8 Population Predicted Steady State PK Exposures (Median with 5th - 95th Percentiles) in Breast Cancer and MGC Patients
Schedule | Primary tumor type | N | Cmin,ss [Steady-state trough serum concentration of trastuzumab] (µg/mL) | Cmax,ss [Maximum steady-state serum concentration of trastuzumab] (µg/mL) | AUCss, 0-21 days (µg.day/mL) | Time to steady-state (week) | Total CL range at steady-state (L/day)
8 mg/kg + 6 mg/kg q3w | Breast cancer | 1195 | 47.4 (5 - 115) | 179 (107 - 309) | 1794 (673 - 3618) | 12 | 0.173 - 0.283
8 mg/kg + 6 mg/kg q3w | MGC | 274 | 32.9 (6.1 - 88.9) | 131 (72.5 - 251) | 1338 (557 - 2875) | 9 | 0.189 - 0.337
4 mg/kg + 2 mg/kg qw | Breast cancer | 1195 | 66.1 (14.9 - 142) | 109 (51.0 - 209) | 1765 (647 - 3578) | 12 | 0.201 - 0.244

Specific Populations

Based on a population pharmacokinetic analysis, no clinically significant differences were observed in the pharmacokinetics of trastuzumab based on age (< 65 (n = 1294); ≥ 65 (n = 288)), race (Asian (n = 264); non-Asian (n = 1324)) and renal impairment (mild (creatinine clearance [CLcr] 60 to 90 mL/min) (n = 636) or moderate (CLcr 30 to 60 mL/min) (n = 133)). The pharmacokinetics of trastuzumab in patients with severe renal impairment, end-stage renal disease with or without hemodialysis, or hepatic impairment is unknown.

Drug Interaction Studies

There have been no formal drug interaction studies performed with Herceptin in humans. Clinically significant interactions between Herceptin and concomitant medications used in clinical trials have not been observed.

Paclitaxel and doxorubicin: Concentrations of paclitaxel and doxorubicin and their major metabolites (i.e., 6-α hydroxyl-paclitaxel [POH], and doxorubicinol [DOL], respectively) were not altered in the presence of trastuzumab when used as combination therapy in clinical trials. Trastuzumab concentrations were not altered as part of this combination therapy.

Docetaxel and carboplatin: When Herceptin was administered in combination with docetaxel or carboplatin, neither the plasma concentrations of docetaxel or carboplatin nor the plasma concentrations of trastuzumab were altered.

Cisplatin and capecitabine: In a drug interaction substudy conducted in patients in ToGA, the pharmacokinetics of cisplatin, capecitabine and their metabolites were not altered when administered in combination with Herceptin.

12.6 Immunogenicity

The observed incidence of anti-drug antibodies is highly dependent on the sensitivity and specificity of the assay. Differences in assay methods preclude meaningful comparisons of the incidence of anti-drug antibodies in the studies described below with the incidence of anti-drug antibodies in other studies, including those of HERCEPTIN or of other trastuzumab products.

Among 903 women with metastatic breast cancer, human anti human antibody (HAHA) to Herceptin was detected in one patient using an enzyme linked immunosorbent assay (ELISA). This patient did not experience an allergic reaction. Samples for assessment of HAHA were not collected in studies of adjuvant breast cancer.

The clinical relevance of the development of anti-trastuzumab antibodies after treatment with HERCEPTIN is not known.

13 NONCLINICAL TOXICOLOGY

13.1 Carcinogenesis, Mutagenesis, Impairment of Fertility

Herceptin has not been tested for carcinogenic potential.

No evidence of mutagenic activity was observed when trastuzumab was tested in the standard Ames bacterial and human peripheral blood lymphocyte mutagenicity assays at concentrations of up to 5000 mcg/mL. In an in vivo micronucleus assay, no evidence of chromosomal damage to mouse bone marrow cells was observed following bolus intravenous doses of up to 118 mg/kg of trastuzumab.

A fertility study was conducted in female Cynomolgus monkeys at doses up to 25 times the weekly recommended human dose of 2 mg/kg of trastuzumab and has revealed no evidence of impaired fertility, as measured by menstrual cycle duration and female sex hormone levels.

14 CLINICAL STUDIES

14.1 Adjuvant Breast Cancer

The safety and efficacy of Herceptin in women receiving adjuvant chemotherapy for HER2 overexpressing breast cancer were evaluated in an integrated analysis of two randomized, open-label, clinical trials (NSABP B31 and NCCTG N9831) with a total of 4063 women at the protocol-specified final overall survival analysis, a third randomized, open-label, clinical trial (HERA) with a total of 3386 women at definitive Disease-Free Survival analysis for one-year Herceptin treatment versus observation, and a fourth randomized, open-label clinical trial with a total of 3222 patients (BCIRG006).

NSABP B31 and NCCTG N9831

In NSABP B31 and NCCTG N9831, breast tumor specimens were required to show HER2 overexpression (3+ by IHC) or gene amplification (by FISH). HER2 testing was verified by a central laboratory prior to randomization (NCCTG N9831) or was required to be performed at a reference laboratory (NSABP B31). Patients with a history of active cardiac disease based on symptoms, abnormal electrocardiographic, radiologic, or left ventricular ejection fraction findings or uncontrolled hypertension (diastolic > 100 mm Hg or systolic > 200 mm Hg) were not eligible.

Patients were randomized (1:1) to receive doxorubicin and cyclophosphamide followed by paclitaxel (AC→paclitaxel) alone or paclitaxel plus Herceptin (AC→paclitaxel + Herceptin). In both trials, patients received four 21-day cycles of doxorubicin 60 mg/m^2 and cyclophosphamide 600 mg/m^2. Paclitaxel was administered either weekly (80 mg/m^2) or every 3 weeks (175 mg/m^2) for a total of 12 weeks in NSABP B31; paclitaxel was administered only by the weekly schedule in NCCTG N9831. Herceptin was administered at 4 mg/kg on the day of initiation of paclitaxel and then at a dose of 2 mg/kg weekly for a total of 52 weeks. Herceptin treatment was permanently discontinued in patients who developed congestive heart failure, or persistent/recurrent LVEF decline [see Dosage and Administration (2.5)]. Radiation therapy, if administered, was initiated after the completion of chemotherapy. Patients with ER+ and/or PR+ tumors received hormonal therapy. The major efficacy outcome measure of the combined efficacy analysis was Disease-Free Survival (DFS), defined as the time from randomization to recurrence, occurrence of contralateral breast cancer, other second primary cancer, or death. An additional efficacy outcome measure was overall survival (OS).

A total of 3752 patients were included in the joint efficacy analysis of DFS following a median follow-up of 2.0 years in the AC→paclitaxel + Herceptin arm. The pre-planned final OS analysis from the joint analysis included 4063 patients and was performed when 707 deaths had occurred after a median follow-up of 8.3 years in the AC→paclitaxel + Herceptin arm. The data from both arms in NSABP B31 and two of the three study arms in NCCTG N9831 were pooled for efficacy analyses.

The patients included in the DFS analysis had a median age of 49 years (range, 22–80 years; 6% > 65 years), 84% were White, 7% Black, 4% Hispanic, and 4% Asian/Pacific Islander. Disease characteristics included 90% infiltrating ductal histology, 38% T1, 91% nodal involvement, 27% intermediate and 66% high grade pathology, and 53% ER+ and/or PR+ tumors.

HERA

In HERA, breast tumor specimens were required to show HER2 overexpression (3+ by IHC) or gene amplification (by FISH) as determined at a central laboratory. Patients with node-negative disease were required to have ≥ T1c primary tumor. Patients with a history of congestive heart failure or LVEF < 55%, uncontrolled arrhythmias, angina requiring medication, clinically significant valvular heart disease, evidence of transmural infarction on ECG, poorly controlled hypertension (systolic > 180 mm Hg or diastolic > 100 mm Hg) were not eligible.

Patients were randomized (1:1:1) upon completion of definitive surgery, and at least four cycles of chemotherapy to receive no additional treatment, or one year of Herceptin treatment or two years of Herceptin treatment. Patients undergoing a lumpectomy had also completed standard radiotherapy. Patients with ER+ and/or PgR+ disease received systemic adjuvant hormonal therapy at investigator discretion. Herceptin was administered with an initial dose of 8 mg/kg followed by subsequent doses of 6 mg/kg once every three weeks. The major efficacy outcome measure was Disease-Free Survival (DFS), defined as in NSABP B31 and NCCTG N9831.

HERA was designed to compare one and two years of once every three week Herceptin treatment versus observation in patients with HER2 positive EBC following surgery, established chemotherapy and radiotherapy (if applicable). A protocol specified interim efficacy analysis comparing one-year Herceptin treatment to observation was performed at a median follow-up duration of 12.6 months in the Herceptin arm.

Among the 3386 patients randomized to the observation (n = 1693) and Herceptin one-year (n = 1693) treatment arms, the median age was 49 years (range 21–80), 83% were White, and 13% were Asian. Disease characteristics: 94% infiltrating ductal carcinoma, 50% ER+ and/or PgR+, 57% node positive, 32% node negative, and in 11% of patients, nodal status was not assessable due to prior neo-adjuvant chemotherapy. Ninety-six percent (1055/1098) of patients with node-negative disease had high-risk features: among the 1098 patients with node-negative disease, 49% (543) were ER– and PgR–, and 47% (512) were ER and/or PgR+ and had at least one of the following high-risk features: pathological tumor size greater than 2 cm, Grade 2–3, or age < 35 years. Prior to randomization, 94% of patients had received anthracycline-based chemotherapy regimens.

After the DFS results comparing observation to one-year Herceptin treatment were disclosed, a prospectively planned analysis that included comparison of one year versus two years of Herceptin treatment at a median follow-up duration of 8 years was performed. Based on this analysis, extending Herceptin treatment for a duration of two years did not show additional benefit over treatment for one year [Hazard Ratios of two-years Herceptin versus one-year Herceptin treatment in the intent to treat (ITT) population for Disease-Free Survival (DFS) = 0.99 (95% CI: 0.87, 1.13), p-value = 0.90 and Overall Survival (OS) = 0.98 (0.83, 1.15); p-value = 0.78].

BCIRG006

In BCIRG006, breast tumor specimens were required to show HER2 gene amplification (FISH+ only) as determined at a central laboratory. Patients were required to have either node-positive disease, or node-negative disease with at least one of the following high-risk features: ER/PR-negative, tumor size > 2 cm, age < 35 years, or histologic and/or nuclear Grade 2 or 3. Patients with a history of CHF, myocardial infarction, Grade 3 or 4 cardiac arrhythmia, angina requiring medication, clinically significant valvular heart disease, poorly controlled hypertension (diastolic > 100 mm Hg), any T4 or N2, or known N3 or M1 breast cancer were not eligible.

Patients were randomized (1:1:1) to receive doxorubicin and cyclophosphamide followed by docetaxel (AC-T), doxorubicin and cyclophosphamide followed by docetaxel plus Herceptin (AC-TH), or docetaxel and carboplatin plus Herceptin (TCH). In both the AC-T and AC-TH arms, doxorubicin 60 mg/m^2 and cyclophosphamide 600 mg/m^2 were administered every 3 weeks for four cycles; docetaxel 100 mg/m^2 was administered every 3 weeks for four cycles. In the TCH arm, docetaxel 75 mg/m^2 and carboplatin (at a target AUC of 6 mg/mL/min as a 30- to 60-minute infusion) were administered every 3 weeks for six cycles. Herceptin was administered weekly (initial dose of 4 mg/kg followed by weekly dose of 2 mg/kg) concurrently with either T or TC, and then every 3 weeks (6 mg/kg) as monotherapy for a total of 52 weeks. Radiation therapy, if administered, was initiated after completion of chemotherapy. Patients with ER+ and/or PR+ tumors received hormonal therapy. Disease-Free Survival (DFS) was the major efficacy outcome measure.

Among 3222 patients, the median age was 49 (range 22 to 74 years; 6% ≥ 65 years). Disease characteristics included 54% ER+ and/or PR+ and 71% node positive. Prior to randomization, all patients underwent primary surgery for breast cancer.

The results for DFS for the integrated analysis of NSABP B31 and NCCTG N9831, HERA, and BCIRG006 and OS results for the integrated analysis of NSABP B31 and NCCTG N9831, and HERA are presented in Table 9. For NSABP B31 and NCCTG N9831, the duration of DFS following a median follow-up of 2.0 years in the AC→TH arm is presented in Figure 4, and the duration of OS after a median follow-up of 8.3 years in the AC→TH arm is presented in Figure 5. The duration of DFS for BCIRG006 is presented in Figure 6. For NSABP B31 and NCCTG N9831, the OS hazard ratio was 0.64 (95% CI: 0.55, 0.74). At 8.3 years of median follow-up [AC→TH], the survival rate was estimated to be 86.9% in the AC→TH arm and 79.4% in the AC→T arm. The final OS analysis results from NSABP B31 and NCCTG N9831 indicate that OS benefit by age, hormone receptor status, number of positive lymph nodes, tumor size and grade, and surgery/radiation therapy was consistent with the treatment effect in the overall population. In patients ≤ 50 years of age (n = 2197), the OS hazard ratio was 0.65 (95% CI: 0.52, 0.81) and in patients > 50 years of age (n = 1866), the OS hazard ratio was 0.63 (95% CI: 0.51, 0.78). In the subgroup of patients with hormone receptor-positive disease (ER-positive and/or PR-positive) (n = 2223), the hazard ratio for OS was 0.63 (95% CI: 0.51, 0.78). In the subgroup of patients with hormone receptor-negative disease (ER-negative and PR-negative) (n = 1830), the hazard ratio for OS was 0.64 (95% CI: 0.52, 0.80). In the subgroup of patients with tumor size ≤ 2 cm (n = 1604), the hazard ratio for OS was 0.52 (95% CI: 0.39, 0.71). In the subgroup of patients with tumor size > 2 cm (n = 2448), the hazard ratio for OS was 0.67 (95% CI: 0.56, 0.80).

Table 9: Efficacy Results from Adjuvant Treatment of Breast Cancer (NSABP B31 and NCCTG N9831, HERA, and BCIRG006)
 | DFS events | DFS Hazard ratio (95% CI) p-value | Deaths (OS events) | OS Hazard ratio p-value
NSABP B31 and NCCTG N9831 [NSABP B31 and NCCTG N9831 regimens: doxorubicin and cyclophosphamide followed by paclitaxel (AC→T) or paclitaxel plus Herceptin (AC→TH).]
AC→TH (n = 1872) [Efficacy evaluable population, for the primary DFS analysis, following a median follow-up of 2.0 years in the AC→TH arm.] (n = 2031) [Efficacy evaluable population, for the final OS analysis, following 707 deaths (8.3 years of median follow-up in the AC→TH arm).] | 133 | 0.48, [Hazard ratio estimated by Cox regression stratified by clinical trial, intended paclitaxel schedule, number of positive nodes, and hormone receptor status.] (0.39, 0.59) p< 0.0001 [stratified log-rank test.] | 289 | 0.64, (0.55, 0.74) p< 0.0001
AC→T (n = 1880) (n = 2032) | 261 |  | 418
HERA [At definitive DFS analysis with median duration of follow-up of 12.6 months in the one-year Herceptin treatment arm.]
Chemo→ Herceptin (n = 1693) | 127 | 0.54 (0.44, 0.67) p< 0.0001 [log-rank test.] | 31 | 0.75 p = NS [NS = non-significant.]
Chemo→ Observation (n = 1693) | 219 |  | 40
BCIRG006 [BCIRG006 regimens: doxorubicin and cyclophosphamide followed by docetaxel (AC→T) or docetaxel plus Herceptin (AC→TH); docetaxel and carboplatin plus Herceptin (TCH).]
TCH (n = 1075) | 134 | 0.67 (0.54 – 0.84) p=0.0006, [A two-sided alpha level of 0.025 for each comparison.] | 56
AC→TH (n = 1074) | 121 | 0.60 (0.48 – 0.76) p< 0.0001, | 49
AC→T (n = 1073) | 180 |  | 80
CI = confidence interval.

Figure 4: Duration of Disease-Free Survival in Patients with Adjuvant Treatment of Breast Cancer (NSABP B31 and NCCTG N9831)

Figure 5: Overall Survival in Patients with Adjuvant Treatment of Breast Cancer (NSABP B31 and NCCTG N9831)

Figure 6: Disease-Free Survival in Patients with Adjuvant Treatment of Breast Cancer (BCIRG006)

Exploratory analyses of DFS as a function of HER2 overexpression or gene amplification were conducted for patients in Studies 2 and 3, where central laboratory testing data were available. The results are shown in Table 10. The number of events in NCCTG N9831 was small with the exception of the IHC 3+/FISH+ subgroup, which constituted 81% of those with data. Definitive conclusions cannot be drawn regarding efficacy within other subgroups due to the small number of events. The number of events in HERA was adequate to demonstrate significant effects on DFS in the IHC 3+/FISH unknown and the FISH+/IHC unknown subgroups.

Table 10: DFS in NCCTG N9831 and HERA for Patients with HER2 Overexpression or Amplification
 | NCCTG N9831 |  | HERA [Median follow-up duration of 12.6 months in the one-year Herceptin treatment arm.]
HER2 Assay Result [IHC by HercepTest, FISH by PathVysion (HER2/CEP17 ratio ≥ 2.0) as performed at a central laboratory.] | Number of Patients | Hazard Ratio DFS (95% CI) | Number of Patients | Hazard Ratio DFS (95% CI)
IHC 3+
FISH (+) | 1170 | 0.42 (0.27, 0.64) | 91 | 0.56 (0.13, 2.50)
FISH (-) | 51 | 0.71 (0.04, 11.79) | 8 | —
FISH Unknown | 51 | 0.69 (0.09, 5.14) | 2258 | 0.53 (0.41, 0.69)
IHC < 3+ / FISH (+) | 174 | 1.01 (0.18, 5.65) | 299 [All cases in this category in HERA were IHC 2+.] | 0.53 (0.20, 1.42)
IHC unknown / FISH (+) | — | — | 724 | 0.59 (0.38, 0.93)

14.2 Metastatic Breast Cancer

The safety and efficacy of Herceptin in treatment of women with metastatic breast cancer were studied in a randomized, controlled clinical trial in combination with chemotherapy (H0648g, n = 469 patients) and an open-label, single agent clinical trial (H0649g, n = 222 patients). Both trials studied patients with metastatic breast cancer whose tumors overexpress the HER2 protein. Patients were eligible if they had 2 or 3 levels of overexpression (based on a 0 to 3 scale) by immunohistochemical assessment of tumor tissue performed by a central testing lab.

Previously Untreated Metastatic Breast Cancer (H0648g)

H0648g was a multicenter, randomized, open-label clinical trial conducted in 469 women with metastatic breast cancer who had not been previously treated with chemotherapy for metastatic disease. Tumor specimens were tested by IHC (Clinical Trial Assay, CTA) and scored as 0, 1+, 2+, or 3+, with 3+ indicating the strongest positivity. Only patients with 2+ or 3+ positive tumors were eligible (about 33% of those screened). Patients were randomized to receive chemotherapy alone or in combination with Herceptin given intravenously as a 4 mg/kg loading dose followed by weekly doses of Herceptin at 2 mg/kg. For those who had received prior anthracycline therapy in the adjuvant setting, chemotherapy consisted of paclitaxel (175 mg/m^2 over 3 hours every 21 days for at least six cycles); for all other patients, chemotherapy consisted of anthracycline plus cyclophosphamide (AC: doxorubicin 60 mg/m^2 or epirubicin 75 mg/m^2 plus 600 mg/m^2 cyclophosphamide every 21 days for six cycles). Sixty-five percent of patients randomized to receive chemotherapy alone in this study received Herceptin at the time of disease progression as part of a separate extension study.

Based upon the determination by an independent response evaluation committee, the patients randomized to Herceptin and chemotherapy experienced a significantly longer median time to disease progression (TTP), a higher overall response rate (ORR), and a longer median duration of response (DoR) as compared with patients randomized to chemotherapy alone. Patients randomized to Herceptin and chemotherapy also had a longer median overall survival (OS) (see Table 11). These treatment effects were observed both in patients who received Herceptin plus paclitaxel and in those who received Herceptin plus AC; however, the magnitude of the effects was greater in the paclitaxel subgroup.

Table 11: H0648g: Efficacy Results in First-Line Treatment for Metastatic Breast Cancer
 | Combined Results |  | Paclitaxel Subgroup |  | AC [AC = Anthracycline (doxorubicin or epirubicin) and cyclophosphamide] Subgroup
 | Herceptin + All Chemotherapy (n = 235) | All Chemotherapy (n = 234) | Herceptin + Paclitaxel (n = 92) | Paclitaxel (n = 96) | Herceptin + AC (n = 143) | AC (n = 138)
Time to Disease Progression (TTP)
Median (months) [Assessed by an independent Response Evaluation Committee] , [Kaplan-Meier Estimate] | 7.2 | 4.5 | 6.7 | 2.5 | 7.6 | 5.7
95% CI | 7, 8 | 4, 5 | 5, 10 | 2, 4 | 7, 9 | 5, 7
p-value [log-rank test] | < 0.0001 |  | < 0.0001 |  | 0.002
Overall Response Rate (ORR)
Events (n) | 45 | 29 | 38 | 15 | 50 | 38
95% CI | 39, 51 | 23, 35 | 28, 48 | 8, 22 | 42, 58 | 30, 46
p-value [χ2-test.] | < 0.001 |  | < 0.001 |  | 0.10
Duration of Response (DoR)
Median (months), | 8.3 | 5.8 | 8.3 | 4.3 | 8.4 | 6.4
25%, 75% Quartile | 6, 15 | 4, 8 | 5, 11 | 4, 7 | 6, 15 | 4, 8
Overall Survival (OS)
Median (months) | 25.1 | 20.3 | 22.1 | 18.4 | 26.8 | 21.4
95% CI | 22, 30 | 17, 24 | 17, 29 | 13, 24 | 23, 33 | 18, 27
p-value | 0.05 |  | 0.17 |  | 0.16

Data from H0648g suggest that the beneficial treatment effects were largely limited to patients with the highest level of HER2 protein overexpression (3+) (see Table 12).

Table 12: Treatment Effects in H0648g as a Function of HER2 Overexpression or Amplification
HER2 Assay Result | Number of Patients (N) | Relative Risk [The relative risk represents the risk of progression or death in the Herceptin plus chemotherapy arm versus the chemotherapy arm.] for Time to Disease Progression (95% CI) | Relative Risk for Mortality (95% CI)
CTA 2+ or 3+ | 469 | 0.49 (0.40, 0.61) | 0.80 (0.64, 1.00)
FISH (+) [FISH testing results were available for 451 of the 469 patients enrolled on study.] | 325 | 0.44 (0.34, 0.57) | 0.70 (0.53, 0.91)
FISH (–) | 126 | 0.62 (0.42, 0.94) | 1.06 (0.70, 1.63)
CTA 2+ | 120 | 0.76 (0.50, 1.15) | 1.26 (0.82, 1.94)
FISH (+) | 32 | 0.54 (0.21, 1.35) | 1.31 (0.53, 3.27)
FISH (–) | 83 | 0.77 (0.48, 1.25) | 1.11 (0.68, 1.82)
CTA 3+ | 349 | 0.42 (0.33, 0.54) | 0.70 (0.51, 0.90)
FISH (+) | 293 | 0.42 (0.32, 0.55) | 0.67 (0.51, 0.89)
FISH (–) | 43 | 0.43 (0.20, 0.94) | 0.88 (0.39, 1.98)

Previously Treated Metastatic Breast Cancer (H0649g)

Herceptin was studied as a single agent in a multicenter, open-label, single-arm clinical trial (H0649g) in patients with HER2 overexpressing metastatic breast cancer who had relapsed following one or two prior chemotherapy regimens for metastatic disease. Of 222 patients enrolled, 66% had received prior adjuvant chemotherapy, 68% had received two prior chemotherapy regimens for metastatic disease, and 25% had received prior myeloablative treatment with hematopoietic rescue. Patients were treated with a loading dose of 4 mg/kg IV followed by weekly doses of Herceptin at 2 mg/kg IV.

The ORR (complete response + partial response), as determined by an independent Response Evaluation Committee, was 14%, with a 2% complete response rate and a 12% partial response rate. Complete responses were observed only in patients with disease limited to skin and lymph nodes. The overall response rate in patients whose tumors tested as CTA 3+ was 18% while in those that tested as CTA 2+, it was 6%.

14.3 Metastatic Gastric Cancer

The safety and efficacy of Herceptin in combination with cisplatin and a fluoropyrimidine (capecitabine or 5-fluorouracil) were studied in patients previously untreated for metastatic gastric or gastroesophageal junction adenocarcinoma (ToGA). In this open-label, multi-center trial, 594 patients were randomized 1:1 to Herceptin in combination with cisplatin and a fluoropyrimidine (FC+H) or chemotherapy alone (FC). Randomization was stratified by extent of disease (metastatic vs. locally advanced), primary site (gastric vs. gastroesophageal junction), tumor measurability (yes vs. no), ECOG performance status (0,1 vs. 2), and fluoropyrimidine (capecitabine vs. 5-fluorouracil). All patients were either HER2 gene amplified (FISH+) or HER2 overexpressing (IHC 3+). Patients were also required to have adequate cardiac function (e.g., LVEF > 50%).

On the Herceptin-containing arm, Herceptin was administered as an IV infusion at an initial dose of 8 mg/kg followed by 6 mg/kg every 3 weeks until disease progression. On both study arms cisplatin was administered at a dose of 80 mg/m^2 Day 1 every 3 weeks for 6 cycles as a 2 hour IV infusion. On both study arms, capecitabine was administered at 1000 mg/m^2 dose orally twice daily (total daily dose 2000 mg/m^2) for 14 days of each 21 day cycle for 6 cycles. Alternatively, continuous intravenous infusion (CIV) 5-fluorouracil was administered at a dose of 800 mg/m^2/day from Day 1 through Day 5 every three weeks for 6 cycles.

The median age of the study population was 60 years (range: 21–83); 76% were male; 53% were Asian, 38% Caucasian, 5% Hispanic, 5% other racial/ethnic groups; 91% had ECOG PS of 0 or 1; 82% had primary gastric cancer and 18% had primary gastroesophageal adenocarcinoma. Of these patients, 23% had undergone prior gastrectomy, 7% had received prior neoadjuvant and/or adjuvant therapy, and 2% had received prior radiotherapy.

The main outcome measure of ToGA was overall survival (OS), analyzed by the unstratified log-rank test. The final OS analysis based on 351 deaths was statistically significant (nominal significance level of 0.0193). An updated OS analysis was conducted at one year after the final analysis. The efficacy results of both the final and the updated analyses are summarized in Table 13 and Figure 7.

Table 13: Overall Survival in ToGA (ITT Population)
 | FC [FC = capecitabine vs. 5-fluorouracil] + Herceptin Arm N = 298 | FC Arm N = 296
Overall Survival (interim analysis)
N (%) | 167 (56.0%) | 184 (62.2%)
Median (months) | 13.5 | 11.0
95% CI | (11.7, 15.7) | (9.4, 12.5)
Hazard Ratio | 0.73
95% CI | (0.60, 0.91)
p-value [Two sided p-value comparing with the nominal significance level of 0.0193.] | 0.0038
Overall Survival (updated)
N (%) | 221 (74.2%) | 227 (76.7%)
Median (months) | 13.1 | 11.7
95% CI | (11.9, 15.1) | (10.3, 13.0)
Hazard Ratio | 0.80
95% CI | (0.67, 0.97)

Figure 7: Updated Overall Survival in Patients with Metastatic Gastric Cancer (ToGA)

An exploratory analysis of OS in patients based on HER2 gene amplification (FISH) and protein overexpression (IHC) testing is summarized in Table 14.

Table 14 Exploratory Analyses by HER2 Status Using Updated Overall Survival Results
 | FC (N = 296) [Two patients on the FC arm who were FISH+ but IHC status unknown were excluded from the exploratory subgroup analyses.] | FC+H (N = 298) [Five patients on the Herceptin-containing arm who were FISH+, but IHC status unknown were excluded from the exploratory subgroup analyses.]
FISH+ / IHC 0, 1+ subgroup (N=133)
No. Deaths / n (%) | 57/71 (80%) | 56/62 (90%)
Median OS Duration (mos.) | 8.8 | 8.3
95% CI (mos.) | (6.4, 11.7) | (6.2, 10.7)
Hazard ratio (95% CI) | 1.33 (0.92, 1.92)
FISH+ / IHC2+ subgroup (N=160)
No. Deaths / n (%) | 65/80 (81%) | 64/80 (80%)
Median OS Duration (mos.) | 10.8 | 12.3
95% CI (mos.) | (6.8, 12.8) | (9.5, 15.7)
Hazard ratio (95% CI) | 0.78 (0.55, 1.10)
FISH+ or FISH- / IHC3+ [Includes 6 patients on chemotherapy arm, 10 patients on Herceptin arm with FISH–, IHC3+ and 8 patients on chemotherapy arm, 8 patients on Herceptin arm with FISH status unknown, IHC 3+.] subgroup (N=294)
No. Deaths / n (%) | 104/143 (73%) | 96/151 (64%)
Median OS Duration (mos.) | 13.2 | 18.0
95% CI (mos.) | (11.5, 15.2) | (15.5, 21.2)
Hazard ratio (95% CI) | 0.66 (0.50, 0.87)

16 HOW SUPPLIED/STORAGE AND HANDLING

150 mg Single-dose vial

Herceptin (trastuzumab) for injection 150 mg/vial is supplied in a single-dose vial as a preservative-free, white to pale yellow lyophilized sterile powder, under vacuum. Available in a carton containing one single-dose vial (NDC 50242-132-01) and a carton containing 10 single-dose vials (NDC 50242-132-10).

STORAGE AND HANDLING

Store Herceptin vials in the refrigerator at 2°C to 8°C (36°F to 46°F) until time of reconstitution.

17 PATIENT COUNSELING INFORMATION

Cardiomyopathy

- Advise patients to contact a health care professional immediately for any of the following: new onset or worsening shortness of breath, cough, swelling of the ankles/legs, swelling of the face, palpitations, weight gain of more than 5 pounds in 24 hours, dizziness or loss of consciousness [see Boxed Warning: Cardiomyopathy].

Embryo-Fetal Toxicity

- Advise pregnant women and females of reproductive potential that Herceptin exposure during pregnancy or within 7 months prior to conception can result in fetal harm. Advise female patients to contact their healthcare provider with a known or suspected pregnancy [see Use in Specific Populations (8.1)].
- Advise women who are exposed to Herceptin during pregnancy or who become pregnant within 7 months following the last dose of Herceptin that there is a pregnancy pharmacovigilance program that monitor pregnancy outcomes. Encourage these patients to report their pregnancy to Genentech [see Use in Specific Populations (8.1)].
- Advise females of reproductive potential to use effective contraception during treatment and for 7 months following the last dose of Herceptin [see Use in Specific Populations (8.3)].

HERCEPTIN® [trastuzumab]

Manufactured by:
Genentech, Inc.
A Member of the Roche Group
1 DNA Way
South San Francisco, CA 94080-4990
US License No.1048

Herceptin® is a registered trademark of Genentech, Inc.
©2024 Genentech, Inc.

PRINCIPAL DISPLAY PANEL - 150 mg Vial Carton

NDC 50242-132-01

Herceptin®
trastuzumab
For Injection

150 mg per vial

For Intravenous Infusion
After Reconstitution.

Single-Dose Vial.
Discard Unused Portion.

No preservative.

KEEP REFRIGERATED

Genentech
Rx only

10187107